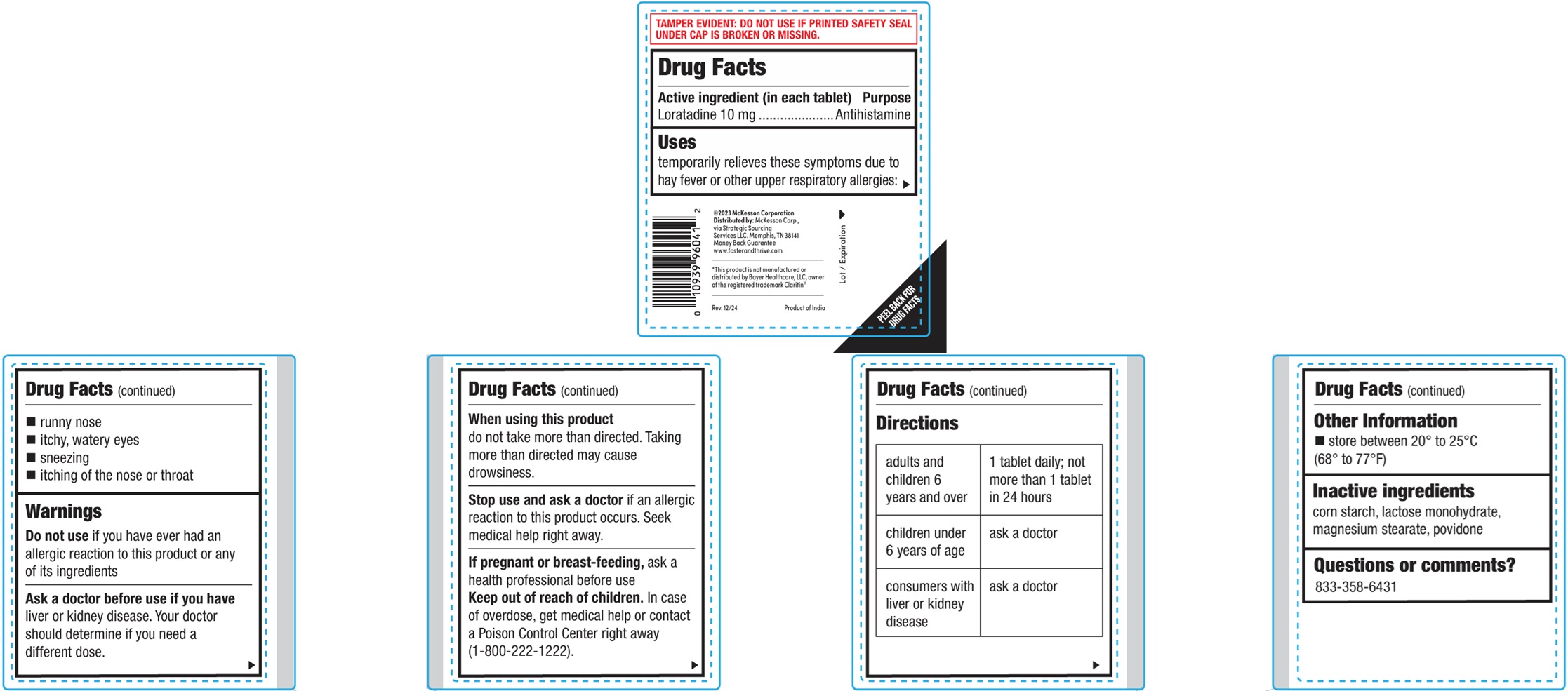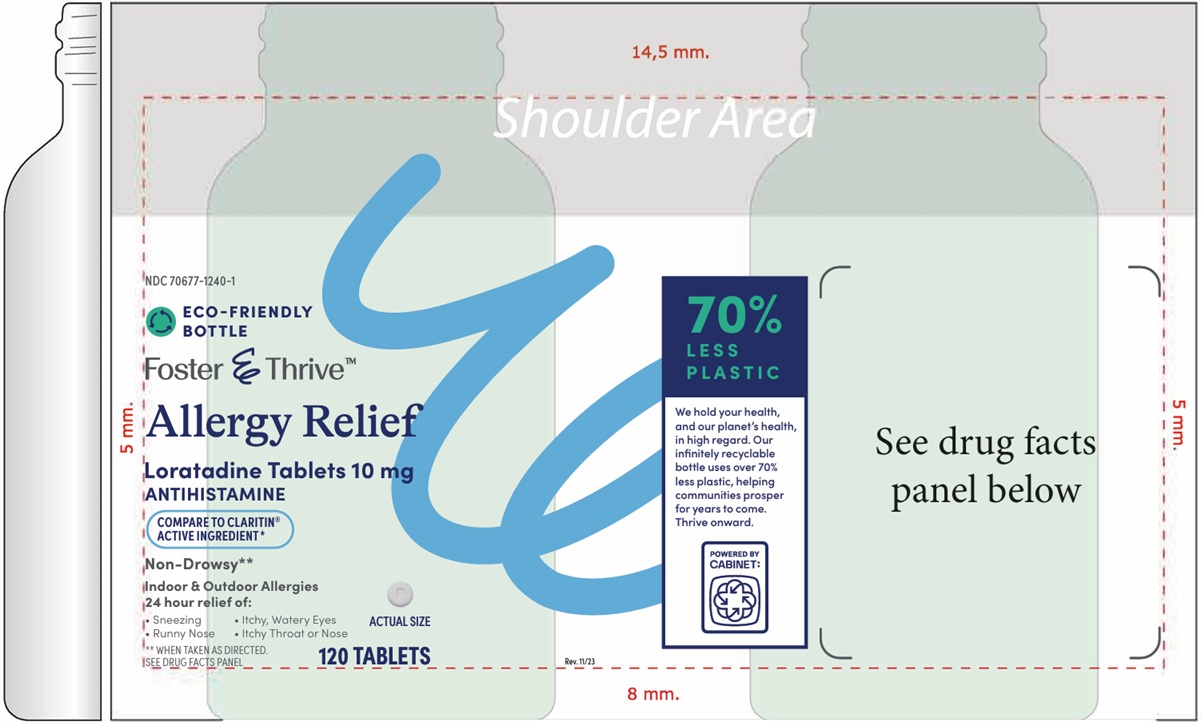 DRUG LABEL: Loratadine
NDC: 70677-1240 | Form: TABLET
Manufacturer: Strategic Sourcing Services, LLC
Category: otc | Type: HUMAN OTC DRUG LABEL
Date: 20260129

ACTIVE INGREDIENTS: LORATADINE 10 mg/1 1
INACTIVE INGREDIENTS: STARCH, CORN; LACTOSE MONOHYDRATE; MAGNESIUM STEARATE; POVIDONE

Loratadine Tablets 10 mg